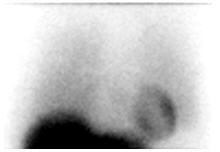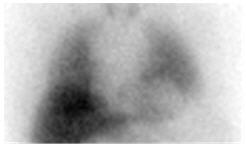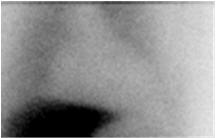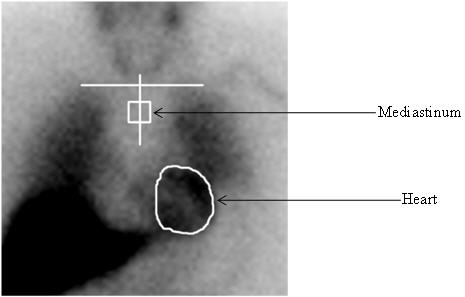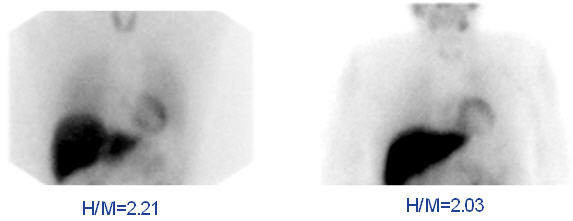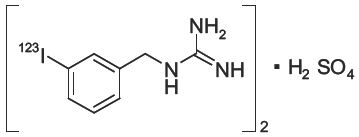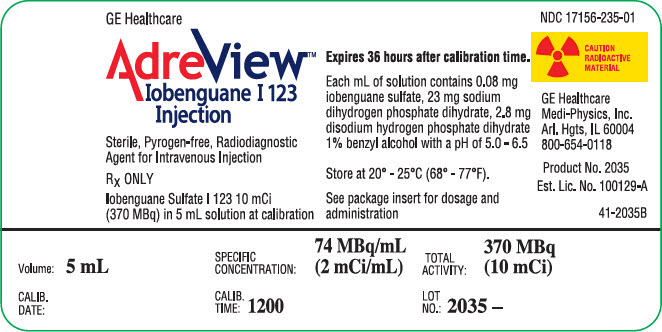 DRUG LABEL: AdreView
NDC: 17156-235 | Form: INJECTION
Manufacturer: Medi-Physics Inc.
Category: prescription | Type: HUMAN PRESCRIPTION DRUG LABEL
Date: 20240110

ACTIVE INGREDIENTS: IOBENGUANE I-123 2 mCi/1 mL
INACTIVE INGREDIENTS: SODIUM PHOSPHATE, MONOBASIC, DIHYDRATE 23 mg/1 mL; SODIUM PHOSPHATE, DIBASIC, DIHYDRATE 2.8 mg/1 mL; BENZYL ALCOHOL 10.3 mg/1 mL

HIGHLIGHTS OF PRESCRIBING INFORMATION

These highlights do not include all the information needed to use AdreView safely and effectively. See full prescribing information for AdreView.
AdreView (Iobenguane I 123 Injection) for Intravenous Use
Initial U.S. Approval: 2008

1 INDICATIONS AND USAGE

AdreView is a radiopharmaceutical agent for gamma-scintigraphy indicated for:

- use in the detection of primary or metastatic pheochromocytoma or neuroblastoma as an adjunct to other diagnostic tests (1.1)
- scintigraphic assessment of sympathetic innervation of the myocardium by measurement of the heart to mediastinum (H/M) ratio of radioactivity uptake in patients with New York Heart Association (NYHA) class II or class III heart failure and left ventricular ejection fraction (LVEF) ≤ 35%. Among these patients, AdreView may be used to help identify patients with lower one and two year mortality risks, as indicated by an H/M ratio ≥ 1.6. (1.2)

Limitations of Use: In patients with congestive heart failure, AdreView utility has not been established for:

- selecting a therapeutic intervention or for monitoring the response to therapy;
- using the H/M ratio to identify a patient with a high risk for death.

2 DOSAGE AND ADMINISTRATION

- AdreView emits radiation and must be handled with appropriate safety measures. (2.1, 2.6)
- Administer thyroid blockade medications to patients at risk for thyroid accumulation of AdreView. (2.2, 5.6)
- Measure patient dose by a suitable radioactivity calibration system immediately prior to administration. (2.4)
- For patients ≥ 16 years of age or < 16 years of age and ≥ 70 kg: administer 10 mCi (370 MBq). (2.4, 2.5)
- For patients < 16 years of age and < 70 kg: amount scaled to the adult reference activity based on weight. (2.5)

3 DOSAGE FORMS AND STRENGTHS

5 mL of sterile solution for intravenous injection in a single use vial (2 mCi/mL at calibration time) (3)

4 CONTRAINDICATIONS

Known hypersensitivity to iobenguane or iobenguane sulfate. (4)

5 WARNINGS AND PRECAUTIONS

- Hypersensitivity reactions have followed AdreView administration. Have anaphylactic and hypersensitivity treatment measures available prior to AdreView administration. (5.1)
- Drugs which block norepinephrine uptake or deplete norepinephrine stores may decrease AdreView uptake. When medically feasible, stop these drugs before AdreView administration and monitor patients for withdrawal signs and symptoms. (5.2)
- AdreView contains benzyl alcohol (10.3 mg/mL) which may cause serious reactions in premature or low birth-weight infants. (5.3)
- Patients with severe renal impairment may have increased radiation exposure and decreased quality of AdreView images. (5.4)
- Failure to block thyroid iodine uptake may result in iodine 123 accumulation in the thyroid. (5.6)

6 ADVERSE REACTIONS

Serious hypersensitivity reactions have been reported following AdreView administration. The most common adverse reactions, dizziness, rash, pruritis, flushing, headache, and injection site hemorrhage occurred in < 1.3% of patients. (6.1, 6.2)

To report SUSPECTED ADVERSE REACTIONS, contact GE Healthcare at 1-800-654-0118 or FDA at 1-800-FDA-1088 or www.fda.gov/medwatch.

7 DRUG INTERACTIONS

Amitryptiline and derivatives, imipramine and derivatives, other antidepressants that inhibit norepinephrine transporter, antihypertensives that deplete norepinephrine stores or inhibit reuptake, sympathomimetic amines and cocaine: Discontinue for 5 biological half-lives prior to AdreView administration (7)

8 USE IN SPECIFIC POPULATIONS

- Pregnancy: May cause fetal harm. (8.1)
- Lactation: Advise a lactating woman to interrupt breastfeeding and pump and discard breastmilk for at least 6 days after AdreView administration. (8.2)
- Pediatrics: safety and effectiveness have not been established in pediatric patients < 1 month of age or in any pediatric patient with heart failure. (8.4)

FULL PRESCRIBING INFORMATION

1 INDICATIONS AND USAGE

1.1 Pheochromocytoma and Neuroblastoma

AdreView is a radiopharmaceutical indicated for use in the detection of primary or metastatic pheochromocytoma or neuroblastoma as an adjunct to other diagnostic tests.

1.2 Congestive Heart Failure

AdreView is indicated for scintigraphic assessment of sympathetic innervation of the myocardium by measurement of the heart to mediastinum (H/M) ratio of radioactivity uptake in patients with New York Heart Association (NYHA) class II or class III heart failure and left ventricular ejection fraction (LVEF) ≤ 35%. Among these patients, AdreView may be used to help identify patients with lower one and two year mortality risks, as indicated by an H/M ratio ≥ 1.6.

Limitations of Use: In patients with congestive heart failure, AdreView utility has not been established for:

- selecting a therapeutic intervention or for monitoring the response to therapy;
- using the H/M ratio to identify a patient with a high risk for death.

2 DOSAGE AND ADMINISTRATION

2.1 Radiation Safety

AdreView emits radiation and must be handled with appropriate safety measures to minimize radiation exposure to clinical personnel and patients. Radiopharmaceuticals should be used by or under the control of physicians who are qualified by specific training and experience in the safe use and handling of radionuclides, and whose experience and training have been approved by the appropriate government agency authorized to license the use of radionuclides. AdreView dosing is based upon the radioactivity determined using a suitable calibration system immediately prior to administration.

To minimize radiation dose to the bladder, prior to and following AdreView administration, encourage hydration to permit frequent voiding. Encourage the patient to void frequently for the first 48 hours following AdreView administration [see Clinical Pharmacology (12.2)].

2.2 Thyroid Blockade

Before administration of AdreView to patients at risk for thyroid accumulation of the drug, administer Potassium Iodide Oral Solution or Lugol's Solution (equivalent to 100 mg iodide for adults, body-weight adjusted for children) or potassium perchlorate (400 mg for adults, body-weight adjusted for children) to block uptake of iodine 123 by the patient's thyroid. Administer the blocking agent at least one hour before the dose of AdreView [see Warnings and Precautions (5.6)]. Individualize thyroid blockade; for example, the blockade may not be necessary for patients who have undergone thyroidectomy or those with a very limited life expectancy.

2.3 Preparation and Administration

- Assess pregnancy status before administering AdreView to a female of reproductive potential.
- Inspect the AdreView vial for particulate matter and discoloration prior to administration. Use aseptic procedures and a radiation shielding syringe during administration. Administer the dose as an intravenous injection over 1 to 2 minutes. A subsequent injection of 0.9% sodium chloride may be used to ensure full delivery of the dose.

2.4 Recommended Dose for Adults

For adults (≥ 16 years of age), the recommended dose is 10 mCi (370 MBq) [see Clinical Studies (14.1, 14.2)].

2.5 Recommended Dose for Pediatric Patients

For pediatric patients < 16 years of age weighing ≥ 70 kg, the recommended dose is 10 mCi (370 MBq) [see Clinical Studies (14.1)].

For pediatric patients < 16 years of age weighing < 70 kg, the recommended dose should be calculated according to patient body weight as shown in Table 1 [see Clinical Studies (14.1)]. The benzyl alcohol in AdreView may cause serious adverse reactions in premature or low birth-weight infants [see Warnings and Precautions (5.3) and Use in Specific Populations (8.4)].

Table 1. AdreView Dose Preparation for Pediatric Patients [Based on a reference activity for an adult scaled to body weight according to the schedule proposed by the European Association of Nuclear Medicine Paediatric Task Group.]
Weight (kg) | Fraction of adult activity | AdreView (mCi) pediatric dose | AdreView (MBq) pediatric dose
3 | 0.1 | 1 | 37
4 | 0.14 | 1.4 | 52
6 | 0.19 | 1.9 | 70
8 | 0.23 | 2.3 | 85.1
10 | 0.27 | 2.7 | 99.9
12 | 0.32 | 3.2 | 118.4
14 | 0.36 | 3.6 | 133.2
16 | 0.4 | 4 | 148
18 | 0.44 | 4.4 | 162.8
20 | 0.46 | 4.6 | 170.2
22 | 0.5 | 5 | 185
24 | 0.53 | 5.3 | 196.1
26 | 0.56 | 5.6 | 207.2
28 | 0.58 | 5.8 | 214.6
30 | 0.62 | 6.2 | 229.4
32 | 0.65 | 6.5 | 240.5
34 | 0.68 | 6.8 | 251.6
36 | 0.71 | 7.1 | 262.7
38 | 0.73 | 7.3 | 270.1
40 | 0.76 | 7.6 | 281.2
42 | 0.78 | 7.8 | 288.6
44 | 0.8 | 8 | 296
46 | 0.82 | 8.2 | 303.4
48 | 0.85 | 8.5 | 314.5
50 | 0.88 | 8.8 | 325.6
52 | 0.9 | 9 | 333
54 | 0.9 | 9 | 333
56 | 0.92 | 9.2 | 340.4
58 | 0.92 | 9.2 | 340.4
60 | 0.96 | 9.6 | 355.2
62 | 0.96 | 9.6 | 355.2
64 | 0.98 | 9.8 | 362.6
66 | 0.98 | 9.8 | 362.6
68 | 0.99 | 9.9 | 366.3

2.6 Radiation Dosimetry

The estimated absorbed radiation doses to adults and children from intravenous administration of AdreView are as shown in Table 2:

Table 2. Estimated Absorbed Radiation Dose from AdreView
ORGAN / TISSUE |  |  | ABSORBED DOSE PER UNIT ADMINISTERED ACTIVITY
ORGAN / TISSUE |  |  | ADULT |  | 15-YEAR OLD |  | 10-YEAR OLD |  | 5-YEAR OLD |  | 1-YEAR OLD |  | NEONATES
ORGAN / TISSUE |  |  | μGy/ MBq | rad/mCi | μGy/ MBq | rad/mCi | μGy/ MBq | rad/mCi | μGy/ MBq | rad/mCi | μGy/ MBq | rad/mCi | μGy/ MBq | rad/mCi
Adrenals |  |  | 16 | 0.059 | 21 | 0.078 | 31 | 0.115 | 42 | 0.155 | 67 | 0.248 | 111 | 0.411
Brain |  |  | 3.9 | 0.014 | 4.9 | 0.018 | 8.1 | 0.030 | 13 | 0.048 | 24 | 0.089 | 55.9 | 0.207
Breast |  |  | 4.7 | 0.017 | 5.9 | 0.022 | 9.4 | 0.035 | 15 | 0.056 | 28 | 0.104 | 65.3 | 0.242
Gallbladder |  |  | 20 | 0.074 | 24 | 0.089 | 34 | 0.126 | 51 | 0.189 | 95 | 0.352 | 200 | 0.740
GI Tract | Stomach Wall |  | 7.6 | 0.028 | 10 | 0.037 | 17 | 0.063 | 27 | 0.100 | 51 | 0.189 | 114 | 0.422
GI Tract | Small Intestine Wall |  | 7.7 | 0.028 | 9.8 | 0.036 | 16 | 0.059 | 25 | 0.093 | 46 | 0.170 | 104 | 0.385
GI Tract | Colon Wall |  | 8.1 | 0.030 | 10 | 0.037 | 16 | 0.059 | 26 | 0.096 | 46 | 0.170 | 104.3 | 0.386
GI Tract | Upper Large Intestine Wall |  | 8.4 | 0.031 | 11 | 0.041 | 18 | 0.067 | 30 | 0.111 | 53 | 0.196 | 119 | 0.440
GI Tract | Lower Large Intestine Wall |  | 7.7 | 0.028 | 9.6 | 0.036 | 15 | 0.056 | 21 | 0.078 | 38 | 0.141 | 84.9 | 0.314
Heart Wall |  |  | 18 | 0.067 | 23 | 0.085 | 35 | 0.130 | 53 | 0.196 | 94 | 0.348 | 182 | 0.673
Kidneys |  |  | 13 | 0.048 | 16 | 0.059 | 24 | 0.089 | 35 | 0.130 | 59 | 0.218 | 132 | 0.488
Liver |  |  | 67 | 0.248 | 87 | 0.322 | 130 | 0.481 | 180 | 0.666 | 330 | 1.221 | 720 | 2.664
Lungs |  |  | 16 | 0.059 | 23 | 0.085 | 32 | 0.118 | 48 | 0.178 | 89 | 0.329 | 215 | 0.796
Muscles |  |  | 6 | 0.022 | 7.6 | 0.028 | 12 | 0.044 | 17 | 0.063 | 33 | 0.122 | 75.1 | 0.278
Esophagus |  |  | 6 | 0.022 | 7.6 | 0.028 | 11 | 0.041 | 18 | 0.067 | 32 | 0.118 | 72.2 | 0.267
Osteogenic Cells |  |  | 16 | 0.059 | 21 | 0.078 | 31 | 0.115 | 47 | 0.174 | 100 | 0.370 | 254 | 0.940
Ovaries |  |  | 7.9 | 0.029 | 10 | 0.037 | 15 | 0.056 | 22 | 0.081 | 41 | 0.152 | 92.3 | 0.342
Pancreas |  |  | 12 | 0.044 | 15 | 0.056 | 25 | 0.093 | 39 | 0.144 | 68 | 0.252 | 143 | 0.529
Red marrow |  |  | 5.6 | 0.021 | 6.8 | 0.025 | 10 | 0.037 | 15 | 0.056 | 30 | 0.111 | 89.5 | 0.331
Skin |  |  | 3.7 | 0.014 | 4.4 | 0.016 | 7.1 | 0.026 | 11 | 0.041 | 21 | 0.078 | 53.1 | 0.196
Spleen |  |  | 20 | 0.074 | 27 | 0.100 | 42 | 0.155 | 64 | 0.237 | 110 | 0.407 | 282 | 1.043
Testes |  |  | 5.4 | 0.020 | 7.1 | 0.026 | 11 | 0.041 | 16 | 0.059 | 30 | 0.111 | 69.9 | 0.259
Thymus |  |  | 6 | 0.022 | 7.6 | 0.028 | 11 | 0.041 | 18 | 0.067 | 32 | 0.118 | 72.2 | 0.267
Thyroid |  |  | 4.7 | 0.017 | 6.1 | 0.023 | 9.9 | 0.037 | 16 | 0.059 | 30 | 0.111 | 69.4 | 0.257
Urinary Bladder Wall |  |  | 66 | 0.244 | 84 | 0.311 | 110 | 0.407 | 110 | 0.407 | 200 | 0.740 | 478.0 | 1.769
Uterus |  |  | 11 | 0.041 | 14 | 0.052 | 21 | 0.078 | 28 | 0.104 | 51 | 0.189 | 110.0 | 0.407
Whole Body |  |  | 8.1 | 0.030 | 10 | 0.037 | 16 | 0.059 | 24 | 0.089 | 44 | 0.163 | 104.0 | 0.385
EFFECTIVE DOSE | µSv/MBq |  | 13.7 |  | 18.1 |  | 26.7 |  | 37.6 |  | 68 |  | 162
EFFECTIVE DOSE | mSv/mCi |  | 0.507 |  | 0.670 |  | 0.988 |  | 1.39 |  | 2.52 |  | 6
*OLINDA/EXM calculation based on biodistribution data from Swanson et al. and Publication 53 of the ICRP (International Commission on Radiological Protection) [Annals of the ICRP 1987; 18 (1-4): 329-331]

The effective dose resulting from an administered activity amount of 10 mCi is 5.07 mSv in an adult.

2.7 Imaging Guidelines

Pheochromocytoma and Neuroblastoma

Begin whole body planar scintigraphy imaging 24 ± 6 hours following administration of AdreView. Single photon emission computed tomography (SPECT) may be performed following planar scintigraphy, as appropriate [see Clinical Studies (14.1)].

Congestive Heart Failure

Begin anterior planar imaging of the chest at 4 hours (± 10 minutes) following administration of AdreView. Single photon emission computed tomography (SPECT) can then be performed. The recommended collimator for all imaging is a low-energy high-resolution. The recommended matrix for planar images is 128×128. The camera should be positioned to include the entire heart and as much of the upper chest as possible within the field of view [see Clinical Studies (14.2)].

2.8 Estimation of the H/M Ratio among Patients with Congestive Heart Failure

Initial evaluation of cardiac AdreView images involves visual examination of the location, pattern and intensity of cardiac radioactivity uptake to guide quantitative assessment (see Step 1 below). Perform quantitative assessment of radioactivity uptake in terms of the heart/mediastinum ratio (H/M) on anterior planar images of the chest (see Step 2 below).

Step 1. Visual Guidelines for AdreView Cardiac Uptake on Anterior Planar Chest Images

- a. Normal:
  Distinct visualization of the left ventricular myocardium in the left lower chest, with greater uptake in the heart than in the adjacent lungs and mediastinum (Figure 1).
- Figure 1. Normal anterior planar AdreView image of the chest
- b. Abnormal:
  Homogeneously or heterogeneously decreased cardiac uptake, with indistinct or absent visualization of the left ventricular myocardium. Cardiac activity is usually less than or equal to that of the adjacent left lung (Figure 2a). In extreme cases, little or no AdreView uptake is seen in the left lower chest (Figure 2b).
- Figure 2. Abnormal anterior planar AdreView images of the chest: a) Heterogeneously reduced cardiac uptake; b) Absent cardiac uptake
  Figure 2a
  Figure 2b

Step 2. Quantitate AdreView Cardiac Uptake

The AdreView H/M ratio is determined from the activity in heart (H) and mediastinum (M) regions of interest (ROIs) drawn on the anterior planar chest image (Figure 3) using the following procedure:

- Draw an irregular ROI defining the epicardial border of the heart. If the epicardial border cannot be defined because all or the majority of the myocardium is not visualized, draw the ROI based upon the presumed location of the heart, using the medial aspects of the left and right lower lung for anatomical guidance.
- Draw a horizontal line to mark the estimated location of the lung apices. If the most superior aspect of the image does not include the lung apices (because of limited field of view for a small gamma camera), draw this line at the top of the image display.
- Draw a vertical line approximately equidistant from the medial aspects of the right and left lung.
- Examine the counts for the 12 pixels along the vertical line starting 4 pixels below the intersection point with the horizontal line determined in step 2, and identify the pixel with the lowest counts. If more than one pixel has this same number of counts, choose the most superiorly located pixel.
- Using the pixel defined in step 4 as the center, draw a square ROI of 7×7 dimensions.
- Calculate the H/M ratio by dividing the counts/pixel in the total myocardium ROI determined in step 1 by the counts/pixel in the 7×7 pixel mediastinal ROI determined in step 5.

Figure 3. Illustration of creation of regions of interest for determination of the H/M ratio

Step 3. Interpretation of AdreView H/M Ratio

The expected range for AdreView H/M ratio is 1.0 to 2.4 [see Clinical Studies (14.2)].

Figure 4. Examples of AdreView Images in Subjects with Lower One and Two Year Mortality Risk

3 DOSAGE FORMS AND STRENGTHS

Single use vials containing 5 mL solution for intravenous injection (2 mCi/mL at calibration time).

4 CONTRAINDICATIONS

AdreView is contraindicated in patients with known hypersensitivity to iobenguane or iobenguane sulfate.

5 WARNINGS AND PRECAUTIONS

5.1 Hypersensitivity Reactions

Hypersensitivity reactions have been reported following AdreView administration. Prior to administration, question the patient for a history of prior reactions to iodine, an iodine-containing contrast agent or other products containing iodine. If the patient is known or strongly suspected to have hypersensitivity to iodine, an iodine-containing contrast agent or other products containing iodine, the decision to administer AdreView should be based upon an assessment of the expected benefits compared to the potential hypersensitivity risks. Have anaphylactic and hypersensitivity treatment measures available prior to AdreView administration [see Adverse Reactions (6.2)].

5.2 Imaging Errors due to Concomitant Medications and Risks Associated with Withdrawal of Medications

Many medications have the potential to interfere with AdreView imaging and review of the patient's medications is required prior to AdreView dosing due to the risk for unreliable imaging results. If the AdreView imaging information is essential for clinical care, consider the withdrawal of the following categories of medications if the withdrawal can be accomplished safely: antihypertensives that deplete norepinephrine stores or inhibit reuptake (e.g., reserpine, labetalol), antidepressants that inhibit norepinephrine transporter function (e.g., amitriptyline and derivatives, imipramine and derivatives, selective serotonin reuptake inhibitors), and sympathomimetic amines (e.g., phenylephrine, phenylpropanolamine, pseudoephedrine and ephedrine). The period of time necessary to discontinue any specific medication prior to AdreView dosing has not been established [see Drug Interactions (7)].

Pheochromocytoma and Neuroblastoma

Drugs which interfere with norepinephrine uptake in neuroendocrine tumors may lead to false negative imaging results. When medically feasible, stop these drugs before AdreView administration and monitor patients for the occurrence of clinically significant withdrawal symptoms, especially patients with elevated levels of circulating catecholamines and their metabolites.

Congestive Heart Failure

Many commonly used cardiovascular, pulmonary, and neuropsychiatric medications interfere with AdreView imaging (see above). AdreView imaging should not be performed if discontinuation of these medications would involve risks which outweigh the value of AdreView imaging. In clinical trials, patients were not eligible for AdreView imaging if they were receiving medications in the above categories and the risks for medication withdrawal were unacceptable or if they were not clinically stable (e.g., experiencing continuing chest pain, hemodynamic instability, or clinically significant arrhythmia).

5.3 Risk of Serious Adverse Reactions in Infants due to Benzyl Alcohol Preservative

Serious and fatal adverse reactions including "gasping syndrome" can occur in neonates and infants treated with benzyl alcohol-preserved drugs, including AdreView. The "gasping syndrome" is characterized by central nervous system depression, metabolic acidosis, and gasping respirations. When administering AdreView in infants consider the combined daily metabolic load of benzyl alcohol from all sources including AdreView (contains 10.3 mg of benzyl alcohol per mL) and other drugs containing benzyl alcohol. The minimum amount of benzyl alcohol at which serious adverse reactions may occur is not known [see Use in Specific Populations (8.4)].

5.4 Increased Radiation Exposure in Patients with Severe Renal Impairment

AdreView is cleared by glomerular filtration and is not dialyzable. The radiation dose to patients with severe renal impairment may be increased due to the delayed elimination of the drug. Delayed AdreView clearance may also reduce the target to background ratios and decrease the quality of scintigraphic images. These risks importantly may limit the role of AdreView in the diagnostic evaluation of patients with severe renal impairment. AdreView safety and efficacy have not been established in these patients [see Clinical Pharmacology (12.2)].

5.5 Imaging Errors due to Conditions that Affect the Sympathetic Nervous System

Individuals with conditions that affect the sympathetic nervous system, e.g., Parkinsonian syndromes such as Parkinson's disease or multiple system atrophy, may show decreased cardiac uptake of AdreView independent of heart disease.

5.6 Thyroid Accumulation

Failure to block thyroid uptake of iodine 123 may result in an increased long term risk for thyroid neoplasia [see Dosage and Administration (2.2)].

5.7 Hypertension

Assess the patient's pulse and blood pressure before and intermittently for 30 minutes after AdreView administration. AdreView may increase release of norepinephrine from chromaffin granules and produce a transient episode of hypertension, although this was not observed in the clinical studies. Prior to AdreView administration, ensure emergency cardiac and anti-hypertensive treatments are readily available.

6 ADVERSE REACTIONS

6.1 Clinical Study Experience

Because clinical trials are conducted under widely varying conditions, adverse reaction rates observed in the clinical trials of a drug cannot be directly compared to rates in the clinical trials of another drug and may not reflect the rates observed in practice.

During clinical development 1346 patients were exposed to AdreView, 251 patients with known or suspected pheochromocytoma or neuroblastoma, 985 patients with heart failure, and 110 control patients. All patients were monitored for adverse reactions over a 24 hour period following AdreView administration.

Pheochromocytoma and Neuroblastoma

Serious adverse reactions were not observed in the AdreView clinical study. Adverse reactions were all mild to moderate in severity and were predominantly isolated occurrences (≤ 2 patients) of one of the following reactions: dizziness, rash, pruritus, flushing or injection site hemorrhage.

Congestive Heart Failure

No serious adverse reactions to AdreView were observed in clinical studies. Adverse reactions that occurred with a frequency > 1% were associated with the injection site (1.3%), problems such as hematoma and bruising. The other most common reactions were flushing (0.3%) and headache (0.4%). The adverse reactions were predominantly of mild to moderate intensity.

6.2 Postmarketing Experience

Because postmarketing reactions are reported voluntarily from a population of uncertain size, it is not always possible to reliably estimate their frequency or establish a causal relationship to drug exposure.

Hypersensitivity reactions have uncommonly been reported during the postmarketing use of AdreView [see Warnings and Precautions (5.1)].

7 DRUG INTERACTIONS

The following drugs have the potential to decrease the uptake of norepinephrine and cause false negative imaging results: antihypertensives that deplete norepinephrine stores or inhibit reuptake (e.g., reserpine, labetalol), antidepressants that inhibit norepinephrine transporter function (e.g., amitriptyline and derivatives, imipramine and derivatives, selective serotonin reuptake inhibitors), sympathomimetic amines (e.g., phenylephrine, phenylpropanolamine, pseudoephedrine and ephedrine), and cocaine. Clinical studies have not determined which specific drugs may cause false negative imaging results nor whether all drugs in any specific pharmacologic class have the same potential to produce the negative imaging results. Increasing the dose of AdreView will not overcome any potential uptake limiting effect of these drugs. Before AdreView administration, discontinue (for at least 5 biological half-lives) drugs known or expected to reduce norepinephrine uptake, as clinically tolerated.

8 USE IN SPECIFIC POPULATIONS

8.1 Pregnancy

Risk Summary

Radioactive iodine products cross the placenta and can permanently impair fetal thyroid function. Administration of an appropriate thyroid blocking agent is recommended before use of AdreView in a pregnant woman to protect the woman and fetus from accumulation of I 123 [see Dosage and Administration (2.2) ].

There are no available data on AdreView use in pregnant women to evaluate for a drug-associated risk of major birth defects, miscarriage or adverse maternal or fetal outcomes. Animal reproduction studies have not been conducted with iobenguane I 123. All radiopharmaceuticals have the potential to cause fetal harm depending on the fetal stage of development and the magnitude of the radiation dose. Advise pregnant women of the potential risks of fetal exposure to radiation doses with administration of AdreView.

AdreView contains 10.3 mg/mL of benzyl alcohol. Because benzyl alcohol is rapidly metabolized by a pregnant woman, benzyl alcohol exposure in the fetus is unlikely. However, adverse reactions have occurred in premature neonates and low birth weight infants who received intravenously administered benzyl alcohol-containing drugs [see Warnings and Precautions (5.3) and Use in Specific Populations (8.4)].

The estimated background risk of major birth defects and miscarriage for the indicated population(s) is unknown. All pregnancies have a background risk of birth defect, loss, or other adverse outcomes. In the U.S. general population, the estimated background risk of major birth defects and miscarriage in clinically recognized pregnancies is 2 to 4% and 15 to 20%, respectively.

8.2 Lactation

Risk Summary

Iodine 123 (I 123), the radionuclide in AdreView, is present in human milk. There is no information on the effects on the breastfed infant or on milk production. Advise a lactating woman to interrupt breastfeeding and pump and discard breastmilk for at least 6 days (>10 physical half-lives) after AdreView administration in order to minimize radiation exposure to a breastfed infant.

8.4 Pediatric Use

The safety and effectiveness of AdreView have been established in the age groups 1 month to 16 years in patients with known or suspected neuroblastoma [see Clinical Studies (14.1)]. Safety and effectiveness in pediatric patients below the age of 1 month or in any pediatric patient with congestive heart failure have not been established.

Serious adverse reactions including fatal reactions and the "gasping syndrome" occurred in premature neonates and infants in the neonatal intensive care unit who received drugs containing benzyl alcohol as a preservative. In these cases, benzyl alcohol dosages of 99 to 234 mg/kg/day produced high levels of benzyl alcohol and its metabolites in the blood and urine (blood levels of benzyl alcohol were 0.61 to 1.378 mmol/L). Additional adverse reactions included gradual neurological deterioration, seizures, intracranial hemorrhage, hematologic abnormalities, skin breakdown, hepatic and renal failure, hypotension, bradycardia, and cardiovascular collapse. Preterm, low-birth weight infants may be more likely to develop these reactions because they may be less able to metabolize benzyl alcohol. When administering AdreView in infants consider the combined daily metabolic load of benzyl alcohol from all sources including AdreView (contains 10.3 mg of benzyl alcohol per mL) and other drugs containing benzyl alcohol. The minimum amount of benzyl alcohol at which serious adverse reactions may occur is not known [see Warnings and Precautions (5.3)].

8.5 Geriatric Use

In clinical studies of AdreView in heart disease, 27% of subjects were 65-74 years of age and 17% of subjects were 75 years of age or over. No overall differences in safety or effectiveness were observed between these subjects and younger subjects, and other reported clinical experience has not identified differences in responses between the elderly and younger patients, but greater sensitivity of some older individuals cannot be ruled out.

AdreView is excreted by the kidneys, and the risks of adverse reactions, increased radiation dose, and occurrence of falsely negative imaging results, may be greater in patients with severely impaired renal function. Because elderly patients are more likely to have decreased renal function, care should be taken in dose selection and image interpretation. Consider assessment of renal function in elderly patients prior to AdreView administration.

10 OVERDOSAGE

The major manifestations of overdose relate predominantly to increased radiation exposure, with the long term risks for neoplasia.

11 DESCRIPTION

AdreView (Iobenguane I 123 Injection) is a sterile, pyrogen-free radiopharmaceutical for intravenous injection. Each mL contains 0.08 mg iobenguane sulfate, 74 MBq (2 mCi) of I 123 (as iobenguane sulfate I 123) at calibration date and time on the label, 23 mg sodium dihydrogen phosphate dihydrate, 2.8 mg disodium hydrogen phosphate dihydrate and 10.3 mg (1% v/v) benzyl alcohol with a pH of 5.0 – 6.5. Iobenguane sulfate I 123 is also known as I 123 meta-iodobenzlyguanidine sulfate and has the following structural formula:

11.1 Physical Characteristics

Iodine 123 is a cyclotron-produced radionuclide that decays to Te 123 by electron capture and has a physical half-life of 13.2 hours.

Table 3. Principal Radiation Emission Data – Iodine 123
Radiation | Energy Level (keV) | Abundance (%)
Gamma | 159 | 83

11.2 External Radiation

The specific gamma ray constant for iodine 123 is 1.6 R/mCi-hr at 1 cm. The first half value thickness of lead (Pb) for I 123 is 0.04 cm. The relative transmission of radiation emitted by the radionuclide that results from interposition of various thicknesses of Pb is shown in Table 4 (e.g., the use of 2.16 cm Pb will decrease the external radiation exposure by a factor of about 1,000).

Table 4. Reduction in In-air Collision Kerma Caused by Lead Shielding [Calculation based on attenuation and energy-transfer coefficients obtained from National Institute of Standards & Technology Report NISTIR 5632.]
Shield Thickness cm of lead (Pb) | Reduction in In-air Collision Kerma
0.04 | 0.5
0.13 | 10^-1
0.77 | 10^-2
2.16 | 10^-3
3.67 | 10^-4

12 CLINICAL PHARMACOLOGY

12.1 Mechanism of Action

Iobenguane is similar in structure to the antihypertensive drug guanethedine and to the neurotransmitter norepinephrine (NE). Iobenguane is, therefore, largely subject to the same uptake and accumulation pathways as NE. Iobenguane is taken up by the NE transporter in adrenergic nerve terminals and stored in the presynaptic storage vesicles. Iobenguane accumulates in adrenergically innervated tissues such as the adrenal medulla, salivary glands, heart, liver, spleen and lungs as well as tumors derived from the neural crest. By labeling iobenguane with the isotope iodine 123, it is possible to obtain scintigraphic images of the organs and tissues in which the radiopharmaceutical accumulates.

12.2 Pharmacodynamics

AdreView is a diagnostic radiopharmaceutical which contains a small quantity of iobenguane that is not expected to produce a pharmacodynamic effect [see Description (11)]. To minimize radiation dose to the thyroid gland, this organ should be blocked before dosing [see Dosage and Administration (2.2)]. Since iobenguane is excreted mainly via the kidneys, patients with severe renal insufficiency may experience increased radiation exposure and impaired imaging results. Frequent voiding should be encouraged after administration to minimize the radiation dose to the bladder [see Warnings and Precautions (5.4)]. The calculation of the estimated radiation dose is shown in Table 2 [see Dosage and Administration (2.6)].

12.3 Pharmacokinetics

Iobenguane is rapidly cleared from the blood and accumulates in adrenergically innervated tissues [see Clinical Pharmacology (12.1)]. Retention is especially prolonged in highly adrenergically innervated tissues (e.g., the adrenal medulla, heart, and salivary glands).

The majority of the iobenguane dose is excreted unaltered by the kidneys via glomerular filtration. A rapid initial clearance of circulating iobenguane is observed, followed by a slow clearance as iobenguane is released from other compartments. In patients with normal renal function, 70 to 90% of the administered dose is recovered unaltered in urine within 4 days. Iobenguane is not cleared by dialysis [see Warnings and Precautions (5.4)]. Most of the remaining radioactivity recovered in the urine is in the form of the radioiodinated metabolite m-iodohippuric acid (MIHA) (typically ≤ 10%) and free radioiodide (typically ≤ 6%). The enzymatic process responsible for metabolism has not been well characterized and the pharmacologic activity of these metabolites has not been studied. Only a small amount (< 1%) of the injected dose is eliminated via the feces.

13 NONCLINICAL TOXICOLOGY

13.1 Carcinogenesis, Mutagenesis, Impairment of Fertility

Iobenguane hemisulfate was not mutagenic in vitro in the Ames bacterial mutation assay and in the in vitro mouse lymphoma test, and was negative in the in vivo micronucleus test in rats.

Long-term animal studies have not been conducted to evaluate AdreView's carcinogenic potential or potential effects on fertility.

13.2 Animal Toxicology and/or Pharmacology

Iobenguane sulfate testing in dogs revealed electrocardiographic (ECG) changes after administration of 202 times the mg/m^2 conversion of the maximum human dose for a 60 kg adult; the no observable effect level (NOEL) was not determined. When iobenguane was tested in a cell system stably expressing hERG-1 potassium channels, inhibition of potassium channels was not observed at an 80 μM iobenguane concentration and the IC50 was 487 μM.

14 CLINICAL STUDIES

14.1 Pheochromocytoma and Neuroblastoma

The safety and efficacy of AdreView were assessed in an open-label, multicenter, multinational trial of 251 subjects with known or suspected neuroblastoma or pheochromocytoma. Diagnostic efficacy for the detection of metabolically active neuroblastoma or pheochromocytoma was determined by comparison of focal increased radionuclide uptake on planar scintigraphy at 24 ± 6 hours post-administration of AdreView against the definitive diagnosis (standard of truth). Anterior and posterior planar whole-body images, or alternatively whole-body overlapping spot images, were acquired from the head to below the knees. Additional spot images were performed as deemed appropriate at the discretion of the clinical image reviewer. SPECT imaging of the thorax and abdomen was then obtained when possible.

Of the 251 subjects dosed with AdreView, 100 had known or suspected neuroblastoma and 151 had known or suspected pheochromocytoma. The population included 154 adults and 97 pediatric patients; the majority of adults were female (59%), the majority of pediatric subjects were male (58%). The adult subjects had a mean age of 49 years (range 17 to 88 years). The pediatric patients (56 males and 41 females) consisted of 32 infants (1 month up to 2 years of age), 62 children (2 years up to 12 years) and three adolescents (12 years up to 16 years).

The definitive diagnosis (standard of truth) for the presence or absence of metabolically active pheochromocytoma or neuroblastoma was determined by histopathology or, when histopathology was unavailable, a composite of imaging (i.e., CT, MRI, [^131I]-mIBG scintigraphy), plasma/urine catecholamine and/or catecholamine metabolite measurements, and clinical follow-up.

A standard of truth was available for 211 subjects (127 with pheochromocytoma, 84 with neuroblastoma) and this group comprised the diagnostic efficacy population. For 93 of these subjects, the standard of truth was based solely upon histopathology. Of 211 subjects in the efficacy population, all had planar scintigraphy and 167 subjects had SPECT in addition to planar imaging. All images were assessed independently by three readers blinded to all clinical data. Table 5 summarizes the AdreView performance characteristics, by reader.

Table 5. AdreView Planar Imaging: Sensitivity and Specificity
Outcome | Reader A | Reader B | Reader C
Sensitivity (n = 159)
Point estimate | 0.80 | 0.77 | 0.79
95% confidence interval | 0.73 - 0.86 | 0.70 - 0.84 | 0.71 - 0.85
Specificity (n = 52)
Point estimate | 0.77 | 0.73 | 0.69
95% confidence interval | 0.63 - 0.87 | 0.59 - 0.84 | 0.55 - 0.81

Performance characteristics (sensitivity and specificity) of AdreView planar imaging in patients with known or suspected neuroblastoma were similar to those in patients with known or suspected pheochromocytoma. Among the selected patients who also underwent SPECT imaging, similar performance characteristics of AdreView scintigraphy were observed when SPECT plus planar imaging was compared to planar imaging alone.

14.2 Congestive Heart Failure

The safety and efficacy of AdreView were evaluated in two open label, multicenter trials in patients with New York Heart Association (NYHA) class II or III heart failure and left ventricular ejection fraction ≤ 35%. The trials excluded subjects with an acute myocardial infarction within the prior thirty days, subjects with a functioning ventricular pacemaker as well as subjects who had received defibrillation to treat a previous arrhythmic event. Subjects underwent AdreView myocardial imaging (planar and SPECT) and continued standard clinical care; AdreView results were not used in a patient's clinical care. Mortality was assessed for up to two years after AdreView imaging and the results from the trials were analyzed using a pre-specified data integration plan.

AdreView images in each trial were reviewed by three independent readers who assessed the H/M ratio on 3 hour 50 minute post-injection planar scintigraphy. Readers were masked to clinical information and the majority read value was used in analyses. The prognostic performance of the H/M ratio in estimating mortality was analyzed using the pre-specified 1.6 ratio cut-point to distinguish patients with higher risk from those with lower risk; other cut-points were also analyzed.

Within the two trials, 964 patients were enrolled; 80% were men, 83% were categorized as NYHA class II and 17% as class III. The average age was 62 years (range 20 - 90 years of age). Most patients had ischemic heart disease (66%) and a history of smoking (74%). The patients were on a stable regimen of cardiovascular medications, including angiotensin converting enzyme (ACE) inhibitors and/or angiotensin receptor blockers (ARBs) (93%) and beta-blockers (92%). The range of AdreView H/M ratios in these subjects was 1.0-2.4 [mean 1.4 (± 0.2 standard deviation)].

Within the two trials, 94 age-matched control subjects without heart disease were enrolled, 64% were men, average age was 59 years (range 29 - 82 years of age). The range of AdreView H/M ratios in these subjects was 1.1-2.4 [mean 1.8 (± 0.2 standard deviation)].

One Year Results: By 12 months following enrollment, 50 (5%) patients had died, 61 (6%) had missing follow-up information and three patients had missing H/M ratios.

Two Year Results: By 23 months following enrollment (the requirement for designation of two-year follow-up), 96 (10%) patients had died, 201 (21%) patients had missing follow-up information and three patients had missing H/M ratio data.

Table 6 summarizes the mortality results by categories of H/M ratio.

Table 6. AdreView H/M Ratios and One and Two Year [Calculated at 23 months based upon protocol definition for 2-year follow-up] Mortality Rates
Range of H/M Ratio Values (number of patients) | One-year Mortality Rate (%) (95% confidence interval) | Two-year Mortality Rate (%) (95% confidence interval)
≥ 1.6 (201) | 1.0 (0.0, 2.4) | 3.3 (0.7, 5.9)
1.2 – 1.6 (668) | 5.5 (3.8, 7.3) | 11.5 (9.0, 14.0)
< 1.2 (92) | 13.4 (6.4, 20.5) | 22.0 (13.2, 30.8)

H/M Ratio Prognostic Performance Characteristics:

Follow-up mortality results were used to estimate the baseline H/M ratio prognostic performance characteristics. In these estimates, various H/M ratio "cut points" were used to group patients into those with higher versus lower H/M values, such as < 1.6 versus ≥ 1.6. The group of patients who died was examined to determine the probability of these patients having had a lower baseline H/M ratio (sensitivity). The group of patients who survived was examined to determine the probability of these patients having had a higher baseline H/M ratio (specificity). Based upon these results, the prognostic usefulness of any given H/M ratio in a patient was estimated by the positive predictive value (PPV) and the negative predictive value (NPV). The PPV is the probability of death given a lower H/M ratio; the NPV is the probability of survival given a higher H/M ratio.

Table 7 summarizes the performance characteristics by various H/M ratio categories for one year, the time point with the most complete data. Results were similar for the two year follow-up time point analyses.

Table 7. One Year Mortality Outcomes and AdreView Prognostic Performance Characteristics
H/M Group [subjects grouped by H/M ratio cut-off values;] | Subjects (n = 961) | Death [6% discontinued patients are counted as survived (non-events)] | Survival | Sensitivity (%) | Specificity (%) | PPV (%) | NPV (%)
< 1.2 | 92 | 12 | 80 | 24 | 91 | 13 | 96
≥ 1.2 | 869 | 38 | 831 | 24 | 91 | 13 | 96
< 1.4 | 429 | 33 | 396 | 66 | 57 | 8 | 97
≥ 1.4 | 532 | 17 | 515 | 66 | 57 | 8 | 97
< 1.6 | 760 | 48 | 712 | 96 | 22 | 6 | 99
≥ 1.6 | 201 | 2 | 199 | 96 | 22 | 6 | 99
< 1.8 | 914 | 50 | 864 | 100 | 5 | 5 | 100
≥ 1.8 | 47 | 0 | 47 | 100 | 5 | 5 | 100

Cox Proportional Hazards Analyses:

The association of potential risk factors with mortality for up to two years was analyzed in Cox multivariate proportional hazard modeling that included such variables as demographics, hypertension, dyslipidemia, diabetes, cardiovascular medications, smoking, and NYHA classification. The initial model included all pre-specified variables except for H/M ratio and used backward selection of variables found to be significant risk factors of all-cause mortality (p < 0.05) for inclusion in the final model. The final model consisted of the significant variables from the initial model plus the H/M ratio. In addition to age, in the final model, the H/M ratio was found to be a significant risk factor for mortality (Hazard Ratio < 0.08, p < 0.001). Left ventricular ejection fraction and brain natriuretic peptide (BNP) were not included in these models, and AdreView SPECT defect scores were not tested in these models.

16 HOW SUPPLIED/STORAGE AND HANDLING

AdreView is supplied in 10 mL glass vials containing a total volume of 5 mL of solution with a total radioactivity of 370 MBq (10 mCi) at calibration time. Each vial is enclosed in a lead container of appropriate thickness.

NDC 17156-235-01

Storage

Store AdreView at 20°-25°C (68°-77°F); excursions permitted to 15°-30°C (59°-86°F) [see USP]. This product does not contain a preservative. Store within the original lead container or equivalent radiation shielding.

In accordance with USP recommendations Iobenguane I 123 Injection preparations should not be used after the expiration date and time stated on the label.

Handling

This preparation is approved for use by persons licensed by the Illinois Emergency Management Agency pursuant to 32 IL. Adm. Code Section 330.260(a) and 335.4010 or equivalent licenses of the Nuclear Regulatory Commission or an Agreement State.

17 PATIENT COUNSELING INFORMATION

Instruct patients to inform their physician or healthcare provider if they:

1. are pregnant. Advise a pregnant woman of the potential risks of fetal exposure to radiation doses with AdreView [see Use in Specific Populations (8.1)].
2. are breast feeding. Advise a lactating woman to interrupt breastfeeding and pump and discard breastmilk for at least 6 days (>10 physical half-lives) after AdreView administration in order to minimize radiation exposure to a breastfed infant [see Use in Specific Populations (8.2].
3. are sensitive to iodine, an iodine-containing contrast agent or other products that contain iodine.
4. are sensitive to Potassium Iodide Oral Solution, or Lugol's Solution.
5. have reduced renal function.

Instruct patients to increase their level of hydration prior to receiving AdreView and to void frequently for the first 48 hours following AdreView administration.

Manufactured and Distributed by GE Healthcare, Medi-Physics, Inc., Arlington Heights, IL 60004 U.S.A.

AdreView is a trademark of GE Healthcare or one of its subsidiaries.
GE and the GE Monogram are trademarks of General Electric Company.

© 2020 General Electric Company – All rights reserved.

43-2035D

PRINCIPAL DISPLAY PANEL - 5 mL Vial Label

GE Healthcare

AdreView™
Iobenguane I 123
Injection

Sterile, Pyrogen-free, Radiodiagnostic
Agent for Intravenous Injection

RX ONLY

Iobenguane Sulfate I 123 10 mCi
(370 MBq) in 5 mL solution at calibration